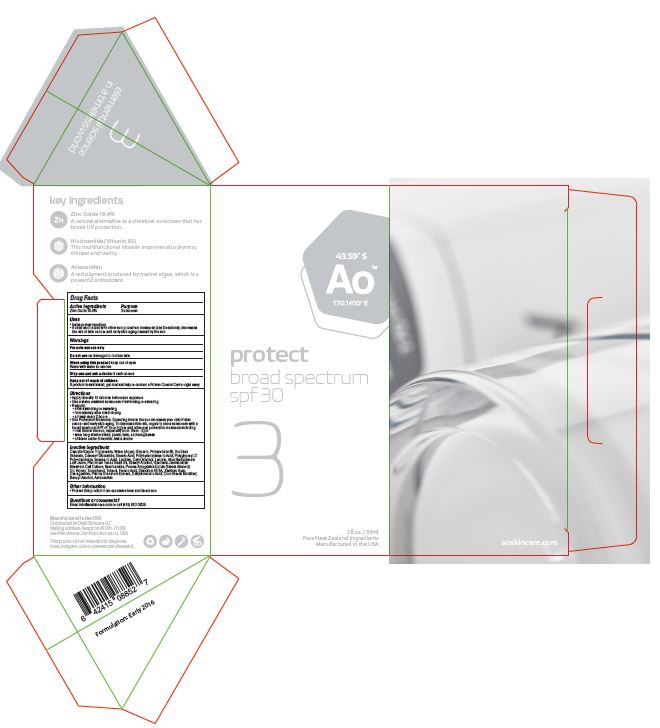 DRUG LABEL: Protect Broad Spectrum SPF 30
NDC: 62742-4166 | Form: CREAM
Manufacturer: Allure Labs Inc
Category: otc | Type: HUMAN OTC DRUG LABEL
Date: 20180209

ACTIVE INGREDIENTS: ZINC OXIDE 189 mg/1 mL
INACTIVE INGREDIENTS: MEDIUM-CHAIN TRIGLYCERIDES; WATER; GLYCERIN; POLYSORBATE 60; STEARIC ACID; CETYL ALCOHOL; SORBITAN MONOSTEARATE; CETEARYL GLUCOSIDE; POLYHYDROXYSTEARIC ACID STEARATE; POLYGLYCERYL-3 POLYDIMETHYLSILOXYETHYL DIMETHICONE (4000 MPA.S); ISOSTEARIC ACID; LECITHIN, SOYBEAN; ALOE; PHORMIUM TENAX SEED OIL; STEARYL ALCOHOL; GARDENIA CORNUTA WHOLE; NIACINAMIDE; PRUNUS AMERICANA FRUIT; HONEY; TOCOPHEROL; TOTAROL; FERULIC ACID; EDETATE DISODIUM; XANTHAN GUM; CARRAGEENAN; PUNICA GRANATUM FLOWER; CORN STARCH 3-E-DODECENYL SUCCINIC ANHYDRIDE MODIFIED; BENZYL ALCOHOL; ASTAXANTHIN

Drug Facts

Active Ingredient:

Zinc Oxide - 18.9%

Purpose: Sunscreen

Uses:

- Helps prevent sunburn.
- If used as directed with other sun protection measures, decreases the risk of skin cancer and early skin aging caused by the sun.

Warnings: For external use only.

Do not use on damaged or broken skin.

When using this product keep out of eyes. Rinse with water to remove.

Stop use and ask a doctor if rash occurs.

Keep out of reach of children if product is swallowed, get medical help or contact a Poison Control right away.

Directions:

- Apply liberally 15 minutes before sun exposure.
- Use a water resistant sunscreen if swimming or sweating.
- Reapply: after swimming or sweating. Immediately after towel drying. At least every 2 hours.
- Sun Protection Measures. Spending time in the sun increases your risk of skin cancer and early skin aging. To decrease this risk, regularly use a sunscreen with a broad spectrum SPF of 15 or higher and other sun protection measures including:
- limit time in the sun, especially from 10am - 2pm.
- wear long sleeves shirts, pants, hats and sunglasses.
- Children under 6 months: Ask a doctor.

OTHER SAFETY INFORMATION

Protect this product from excessive heat and direct sun.

QUESTIONS

Email; info@aoskincare.com or call (415)653-3939

INACTIVE INGREDIENT

Caprylic/Capric Triglyceride, Water (Aqua), Glycerin, Polysorbate 60, Stearic Acid, Cetyl Alcohol, Sorbitan Stearate, Cetearyl Glucoside, Stearic Acid, Polyhydroxystearic acid, Polyglyceryl-3 Polyricinoleate, Isosrearic Acid, Lecithin, Cetyl Alcohol, Lanolin, Aloe Barbadensis Leaf Juice, Phomium Tenax Seed Oil, Stearyl Alcohol, Gardenia Jasminoides Meristem Cell Culture, Niacinamide, Prunus Amygdulus Dulcis (Sweet Almond) Oil, Honey, Tocopherol, Totarol, Ferulic Acid, Disodium EDTA, Xanthan Gum, Carageenan, Punica Granatum Extract, Dihydroacetic Acid, Corn Starch Modified, Benzyl Alcohol, Astaxanthin.

PACKAGE LABEL

Distributed by Distil Skincare LLC

Mailing address: Swapbox ATUP1-1T5DK,

880 Peru Ave #2, San Francisco 94112, USA